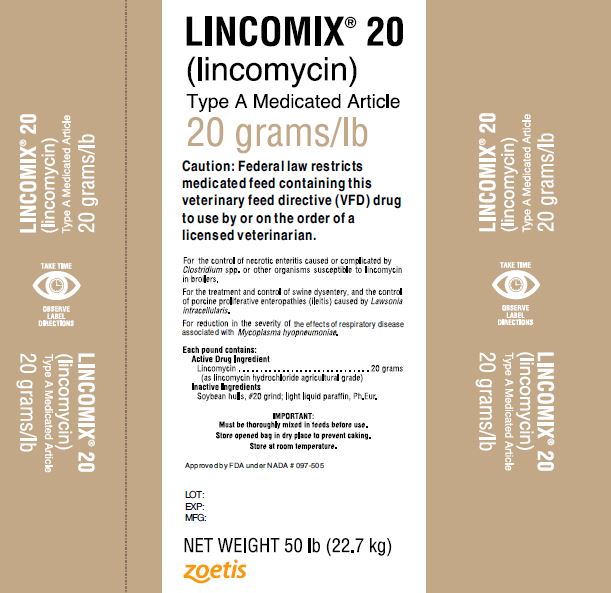 DRUG LABEL: Lincomix 20
NDC: 54771-1439 | Form: GRANULE
Manufacturer: Zoetis Inc.
Category: animal | Type: VFD TYPE A MEDICATED ARTICLE ANIMAL DRUG LABEL
Date: 20221208

ACTIVE INGREDIENTS: LINCOMYCIN HYDROCHLORIDE 20 g/0.453 kg

Lincomix 20

DESCRIPTION

LINCOMIX® 20

(lincomycin)
Type A Medicated Article
20 grams/lb

For the control of necrotic enteritis caused or complicated by Clostridium spp. or other organisms susceptible to lincomycin in broilers.

For the treatment and control of swine dysentery, and the control of porcine proliferative enteropathies (ileitis) caused by Lawsonia intracellularis.

For reduction in the severity of the effects of respiratory disease associated with Mycoplasma hyopneumoniae.

Each pound contains:

Active Drug Ingredient

Lincomycin ………………………………….20 grams

(as lincomycin hydrochloride agricultural grade)

Inactive ingredients

Soybean hulls, #20 grind; light liquid paraffin, Ph.Eur.

IMPORTANT:

Must be thoroughly mixed in feeds before use.

Store open bag in dry place to prevent caking.

Store at room temperature.

Approved by FDA under NADA # 097-505

Caution

Caution: Federal law restricts medicated feed containing this veterinary feed directive (VFD) drug to use by or on the order of a licensed veterinarian.

Broilers

For the control of necrotic enteritis caused or complicated by Clostridium spp. or other organisms susceptible to lincomycin in broilers.

DIRECTIONS FOR USE

For the control of necrotic enteritis:

LINCOMIX 20, 20 grams/lb, should be mixed into the complete feed supplied to broiler chickens so that the final feed contains 2 grams of lincomycin per ton of feed.

MIXING DIRECTIONS

Type C Medicated Feeds

Intermediate Premix; Amount of LINCOMIX 20 per 1000 lb; (454 kg) of Feed Ingredients | Complete Feed; Amount of Intermediate Premix to Provide 2 Grams; of lincomycin per ton of Type C Medicated Feed; lincomycin per ton of feed; 2 grams
50 lbs; 10 lbs; 5 lbs | 2 lb; 10 lbs; 20 lb

WARNING: When using LINCOMIX 20 in approved combinations with other drugs, follow the required withdrawal times for those drugs. No drug withdrawal period is required before slaughter of birds fed LINCOMIX 20 at the approved concentration (2 grams lincomycin per ton of feed).

CAUTION: Not for use in layers, breeders, or turkeys. (For additional Cautions, see below.)

Swine

For the treatment and control of swine dysentery, and the control of porcine proliferative enteropathies (ileitis) caused by Lawsonia intracellularis. For reduction in the severity of the effects of respiratory disease associated with Mycoplasma hyopneumoniae

DIRECTIONS FOR USE

For the treatment of swine dysentery, and the control of porcine proliferative enteropathies (ileitis) caused by Lawsonia intracellularis:

Feed 100 grams of lincomycin per ton of complete feed as the sole ration for three weeks, or until signs of disease (watery, mucoid or bloody stools) disappear.

For the treatment and control of swine dysentery, and the control of porcine proliferative enteropathies (ileitis) caused by Lawsonia intracellularis:

Feed 100 grams of lincomycin per ton of complete feed as the sole rations for three weeks, or until signs of disease (watery, mucoid or bloody stools) disappear, followed by 40 grams of lincomycin per ton.

For the control of swine dysentery and porcine proliferative enteropathies (ileitis) caused by Lawsonia intracellularis: Feed 40 grams of lincomycin per ton of complete feed as the sole ration. For use in animals or on premises with a history of swine dysentery, but where symptoms have not yet occurred.

For reduction in the severity of the effects of respiratory disease associated with Mycoplasma hyopneumoniae: Feed 100-200 grams of lincomycin per ton of complete feed as the sole ration for 21 days.

MIXING DIRECTIONS

Type C Medicated Feeds

For treatment of swine dysentery, and the control of porcine proliferative enteropathies (ileitis) caused by Lawsonia intracellularis:

To make complete feed containing 100 grams of lincomycin, add 5 lbs of LINCOMIX 20 per ton.

For control of swine dysentery and porcine proliferative enteropathies (ileitis) caused by Lawsonia intracellularis:

To make complete feed containing 40 grams of lincomycin, add 2 lbs of LINCOMIX 20 per ton.

For reduction in the severity of the effects of respiratory disease associated with Mycoplasma hyopneumoniae:

To make complete feed containing 100-200 grams of lincomycin, add 5-10 lbs of LINCOMIX 20 per ton.

Additional mixing directions to make complete feed containing 40, 100 or 200 grams of lincomycin per ton are provided below.

MIXING DIRECTIONS

Intermediate Premix; Amount of LINCOMIX 20 per 1000 lb; (454 kg) of Feed Ingredients | Complete Feed; Amount of Intermediate Premix to Provide Desired Grams of lincomycin per ton of Type C Medicated Feed
125 lbs; 100 lbs; 50 lbs | lincomycin per ton of feed 40 grams 100 grams 200 grams 16 lbs 40 lbs 80 lbs; 20 lbs 50 lbs 100 lbs; 40 lbs 100 lbs 200 lbs

WARNING: When using LINCOMIX 20 in approved combinations with other drugs, follow the required withdrawal times for those drugs. No drug withdrawal period is required before slaughter of swine fed LINCOMIX 20 at approved concentrations (40, 100 or 100-200 grams lincomycin per ton of feed).

NOT FOR HUMAN USE

CAUTION: Occasionally, swine fed lincomycin may within the first two days after the onset of treatment develop diarrhea and/or swelling of the anus. On rare occasions, some pigs may show reddening of the skin and irritable behavior. These conditions have been self-correcting within five to eight days without discontinuing the lincomycin treatment. The effects of lincomycin on swine reproductive performance, pregnancy, and lactation have not been determined.

Do not allow rabbits, hamsters, guinea pigs, horses, or ruminants access to feeds containing lincomycin. Ingestion by these species may result in severe gastrointestinal effects.

Good Manufacturing Practices Should Be Observed in Preparing Feeds Containing LINCOMIX 20.

This Includes Appropriate Clean-Out Procedures to Avoid Cross-Contamination.

Restricted Drug (California) – Use Only as Directed

Distributed by:
Zoetis Inc.
Kalamazoo, MI 49007
Made in China
501917
40027872